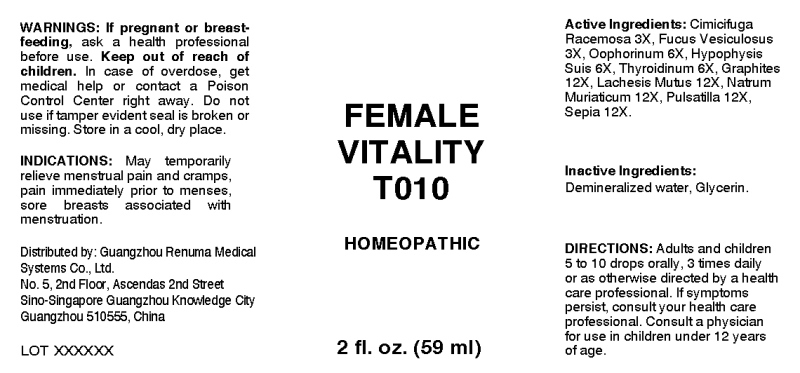 DRUG LABEL: Female Vitality
NDC: 71742-0004 | Form: LIQUID
Manufacturer: Guangzhou Renuma Medical Systems Co., Ltd
Category: homeopathic | Type: HUMAN OTC DRUG LABEL
Date: 20171020

ACTIVE INGREDIENTS: BLACK COHOSH 3 [hp_X]/1 mL; FUCUS VESICULOSUS 3 [hp_X]/1 mL; SUS SCROFA OVARY 6 [hp_X]/1 mL; SUS SCROFA PITUITARY GLAND 6 [hp_X]/1 mL; SUS SCROFA THYROID 6 [hp_X]/1 mL; GRAPHITE 12 [hp_X]/1 mL; LACHESIS MUTA VENOM 12 [hp_X]/1 mL; SODIUM CHLORIDE 12 [hp_X]/1 mL; ANEMONE PRATENSIS 12 [hp_X]/1 mL; SEPIA OFFICINALIS JUICE 12 [hp_X]/1 mL
INACTIVE INGREDIENTS: WATER; ALCOHOL

Drug Facts:

ACTIVE INGREDIENTS:

Cimicifuga Racemosa 3X, Fucus Vesiculosus 3X, Oophorinum (Suis) 6X, Pituitaria Glandula (Suis) 6X, Thyroidinum (Suis) 6X, Graphites 12X, Lachesis Mutus 12X, Natrum Muriaticum 12X, Pulsatilla (Pratensis) 12X, Sepia 12X.

INDICATIONS:

May temporarily relieve menstrual pain and cramps, pain immediately prior to menses, sore breasts associated with menstruation.

WARNINGS:

If pregnant or breast-feeding, ask a health professional before use.

Keep out of reach of children. In case of overdose, get medical help or contact a Poison Control Center right away.

Do not use if tamper evident seal is broken or missing. Store in a cool, dry place.

Keep out of reach of children. In case of overdose, get medical help or contact a Poison Control Center right away.

DIRECTIONS:

Adults and children 5 to 10 drops orally, 3 times daily or as otherwise directed by a health care professional. If symptoms persist, consult your health care professional. Consult a physician for use in children under 12 years of age.

INDICATIONS:

May temporarily relieve menstrual pain and cramps, pain immediately prior to menses, sore breasts associated with menstruation.

INACTIVE INGREDIENTS:

Demineralized water, Glycerin.

QUESTIONS:

Distributed by:

Guangzhou Renuma Medical

Systems Co., Ltd.

No. 5, 2nd Floor, Ascendas 2nd Street

Sino-Singapore Guangzhou Knowledge City

Guangzhou 510555, China

PACKAGE LABEL DISPLAY:

FEMALE

VITALITY

T010

HOMEOPATHIC

2 fl. oz. (59 ml)